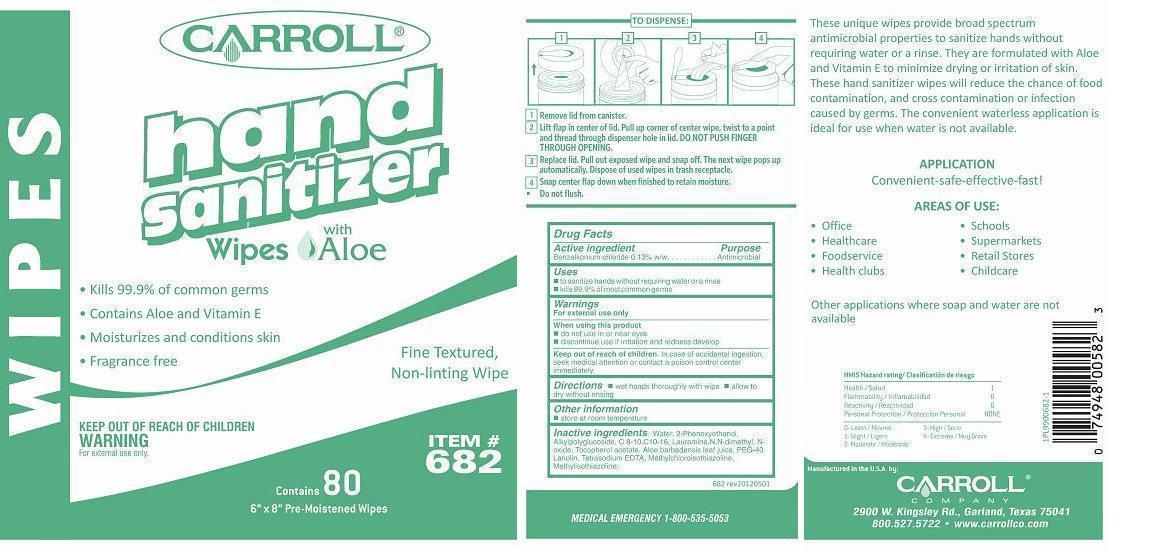 DRUG LABEL: Carroll Hand Sanitizer Wipes with Aloe
NDC: 10685-682 | Form: CLOTH
Manufacturer: Carroll Company
Category: otc | Type: HUMAN OTC DRUG LABEL
Date: 20180131

ACTIVE INGREDIENTS: BENZALKONIUM CHLORIDE 0.0067275 g/1 1
INACTIVE INGREDIENTS: WATER; PHENOXYETHANOL; DECYL GLUCOSIDE; LAURAMINE OXIDE; .ALPHA.-TOCOPHEROL ACETATE; ALOE VERA LEAF; EDETATE SODIUM; METHYLCHLOROISOTHIAZOLINONE; METHYLISOTHIAZOLINONE

Carroll® Hand Sanitizer Wipes with Aloe

Drug Facts

Active ingredient

Benzalkonium chloride 0.13% w/w

Purpose

Antimicrobial

Uses

- to sanitize hands without requiring water or a rinse
- kills 99.9% of most common germs

Warnings

For external use only

When using this product

- do not use in or near eyes
- discontinue use if irritation and redness develop

Keep out of reach of children. In case of accidental ingestion, seek medical attention or contact a poison control center immediately.

Directions

- wet hands thoroughly with wipe
- allow to dry without rinsing

Other information

- store at room temperature

Inactive ingredients

Water, 2-Phenoxyethanol, Alkylpolyglucoside, C 8-10,C10-16, Lauramine,N,N-dimethyl, Noxide, Tocopherol acetate, Aloe barbadensis leaf juice, PEG-40 Lanolin, Tetrasodium EDTA, Methylchloroisothiazoline, Methylisothiazoline.

Manufactured in the U.S.A. by:
CARROL® COMPANY
2900 W. Kingsley Rd., Garland, Texas 75041